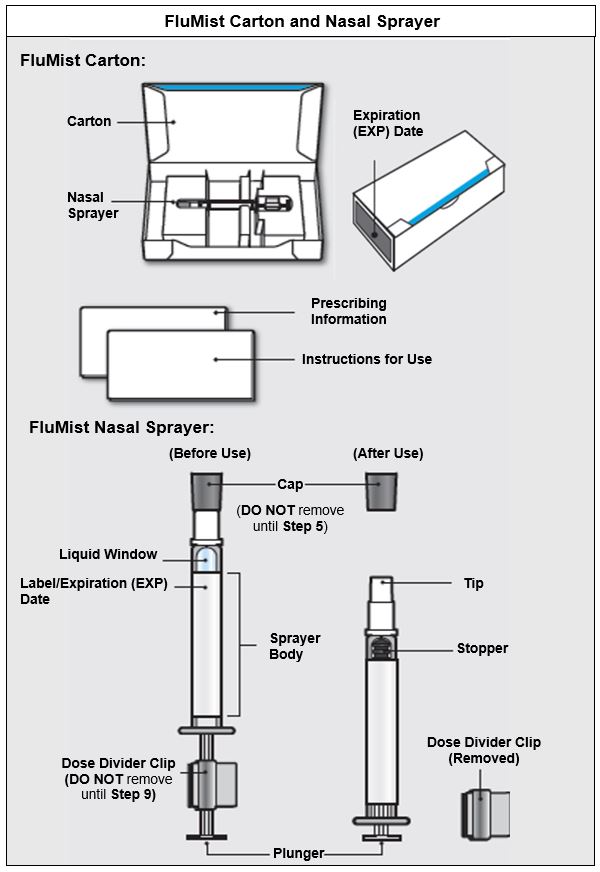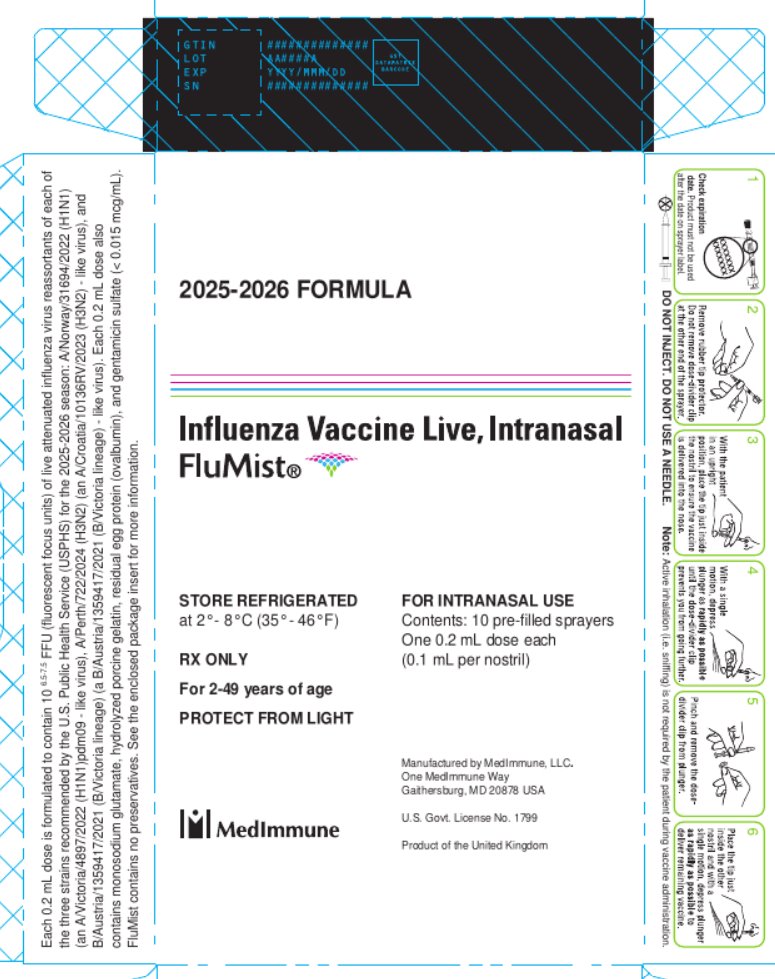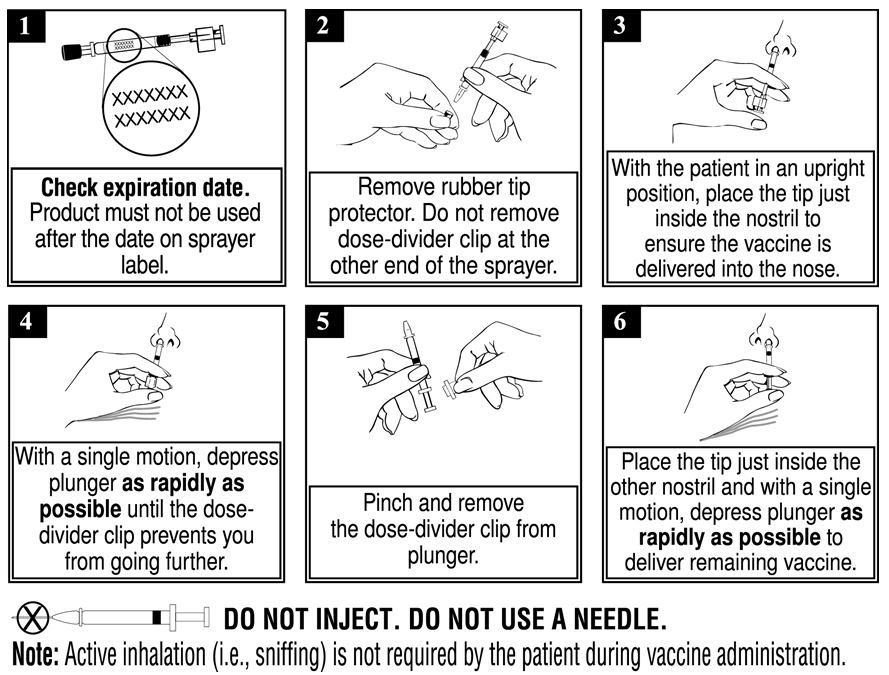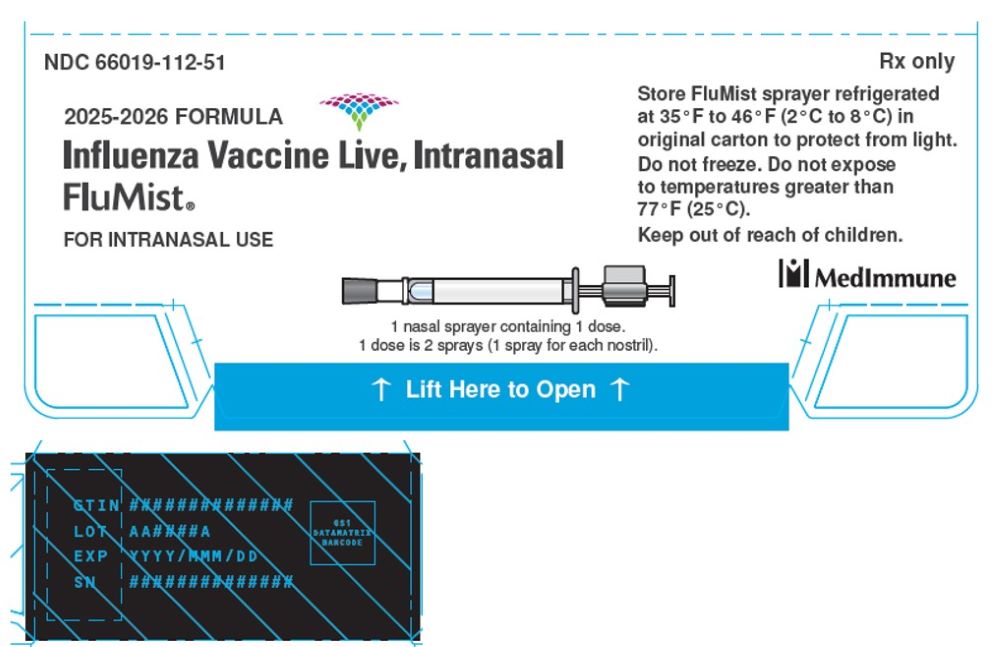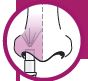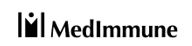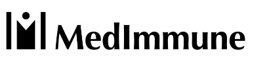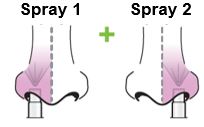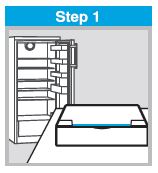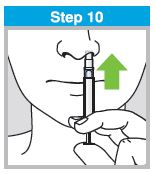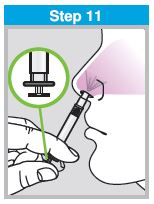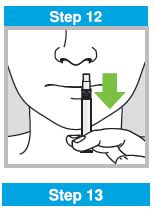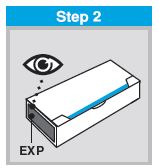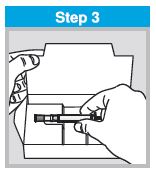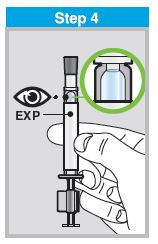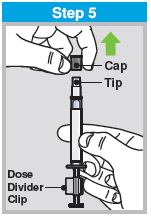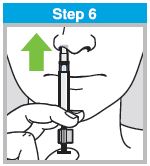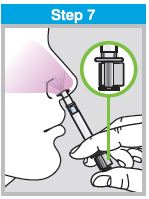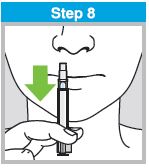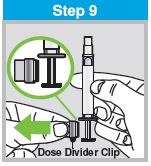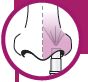 DRUG LABEL: FluMist
NDC: 66019-112 | Form: SPRAY
Manufacturer: MedImmune, LLC
Category: other | Type: VACCINE LABEL
Date: 20250801

ACTIVE INGREDIENTS: INFLUENZA A VIRUS A/NORWAY/31694/2022 (H1N1) LIVE (ATTENUATED) ANTIGEN 10000000 [FFU]/0.2 mL; INFLUENZA A VIRUS A/Perth/722/2024 (H3N2) LIVE (ATTENUATED) ANTIGEN 10000000 [FFU]/0.2 mL; INFLUENZA B VIRUS B/AUSTRIA/1359417/2021 LIVE (ATTENUATED) ANTIGEN 10000000 [FFU]/0.2 mL
INACTIVE INGREDIENTS: MONOSODIUM GLUTAMATE; GELATIN HYDROLYZATE (PORCINE SKIN, MW 3000); ARGININE HYDROCHLORIDE; SUCROSE; WATER; DIBASIC POTASSIUM PHOSPHATE; MONOBASIC POTASSIUM PHOSPHATE

HIGHLIGHTS OF PRESCRIBING INFORMATION

These highlights do not include all the information needed to use FLUMIST® safely and effectively. See full prescribing information for FLUMIST.
FluMist (Influenza Vaccine Live, Intranasal)
Nasal Spray, for intranasal use
2025-2026 Formula
Initial U.S. Approval: 2003

RECENT MAJOR CHANGES

Dosage and Administration (2.2) 09/2024

Warnings and Precautions (5.6) 09/2024

1 INDICATIONS AND USAGE

FluMist is a vaccine indicated for active immunization for the prevention of influenza disease caused by influenza virus subtypes A and type B contained in the vaccine. (1, 11)

FluMist is approved for use in persons 2 through 49 years of age. (1)

2 DOSAGE AND ADMINISTRATION

For intranasal use. (2)

Age | Dose | Schedule
2 years through 8 years | 1 or 2 doses [1 or 2 doses depends on vaccination history as per Advisory Committee on Immunization Practices annual recommendations on prevention and control of influenza with vaccines.] ,; 0.2 mL [Administer as 0.1 mL per nostril.] each | If 2 doses, administer at least 1 month apart
9 years through 49 years | 1 dose, 0.2 mL | -
“-” indicates information is not applicable.

3 DOSAGE FORMS AND STRENGTHS

FluMist is a nasal spray. A single dose is 0.2 mL. (3)

4 CONTRAINDICATIONS

- Do not administer FluMist to persons who have had a severe allergic reaction (e.g., anaphylaxis) to any component of the vaccine including egg protein, or after a previous dose of any influenza vaccine. (4.1, 11)
- Do not administer FluMist to children and adolescents through 17 years of age who are receiving aspirin therapy or aspirin-containing therapy. (4.2, 7.1)

5 WARNINGS AND PRECAUTIONS

- In clinical trials, risks of hospitalization and wheezing were increased in children younger than 2 years of age who received FluMist. (5.1)
- Children younger than 5 years of age with recurrent wheezing and persons of any age with asthma may be at increased risk of wheezing following the administration of FluMist. (5.2)
- If Guillain-Barré syndrome has occurred within 6 weeks of any prior influenza vaccination, the decision to give FluMist should be based on careful consideration of the potential benefits and risks. (5.3)

6 ADVERSE REACTIONS

The most common solicited adverse reactions (≥10% in vaccine recipients and at least 5% greater than in placebo recipients) reported after FluMist were runny nose or nasal congestion (ages 2 years through 49 years), fever over 100°F (children ages 2 years through 6 years), and sore throat (adults ages 18 years through 49 years). (6.1)

To report SUSPECTED ADVERSE REACTIONS, contact MedImmune at 1-877-633-4411 or VAERS at 1-800-822-7967 or http://vaers.hhs.gov.

7 DRUG INTERACTIONS

Antiviral drugs that are active against influenza A and/or B may reduce the effectiveness of FluMist if administered within 48 hours before, or within 2 weeks after, receipt of the vaccine. (7.2)

8 USE IN SPECIFIC POPULATIONS

In clinical trials, in children 6 through 23 months of age, FluMist was associated with an increased risk of hospitalization and wheezing. (8.4)

FULL PRESCRIBING INFORMATION

1 INDICATIONS AND USAGE

FluMist is a vaccine indicated for active immunization for the prevention of influenza disease caused by influenza virus subtypes A and type B contained in the vaccine [see Description (11)].

FluMist is approved for use in persons 2 through 49 years of age.

2 DOSAGE AND ADMINISTRATION

For intranasal use.

2.1 Dosing Information

Administer FluMist according to the following schedule:

Age | Dose | Schedule
2 years through 8 years | 1 or 2 doses [1 or 2 doses depends on vaccination history as per Advisory Committee on Immunization Practices annual recommendations on prevention and control of influenza with vaccines.] , 0.2 mL [Administer as 0.1 mL per nostril.] each | If 2 doses, administer at least 1 month apart
9 years through 49 years | 1 dose, 0.2 mL | -
“-” indicates information is not applicable.

2.2 Administration Instructions

Each sprayer contains a single dose (0.2 mL) of FluMist; administer approximately one half of the contents of the single-dose intranasal sprayer into each nostril.

When administered by a healthcare provider in a healthcare setting, refer to Figure 1 for step-by-step administration instructions. Following administration, dispose of the sprayer according to the standard procedures for medical waste (e.g., sharps container or biohazard container).

Instruct vaccine recipients or caregivers who administer FluMist to follow the directions provided in the “Instructions for Use” for administration and disposal of FluMist. Individuals 2 through 17 years of age should not self‑administer FluMist.

Figure 1

3 DOSAGE FORMS AND STRENGTHS

FluMist is a nasal spray. A single dose is 0.2 mL.

4 CONTRAINDICATIONS

4.1 Severe Allergic Reactions

Do not administer FluMist to persons who have had a severe allergic reaction (e.g., anaphylaxis) to any component of the vaccine [see Description (11)] including egg protein, or after a previous dose of any influenza vaccine.

4.2 Concomitant Aspirin Therapy and Reye’s Syndrome in Children and Adolescents

Do not administer FluMist to children and adolescents through 17 years of age who are receiving aspirin therapy or aspirin-containing therapy because of the association of Reye’s syndrome with aspirin and wild-type influenza infection [see Drug Interactions (7.1)].

5 WARNINGS AND PRECAUTIONS

5.1 Risks of Hospitalization and Wheezing in Children Younger than 24 Months of Age

In clinical trials, risks of hospitalization and wheezing were increased in children younger than 2 years of age who received FluMist [see Adverse Reactions (6.1)].

5.2 Asthma, Recurrent Wheezing, and Active Wheezing

Children younger than 5 years of age with recurrent wheezing and persons of any age with asthma may be at increased risk of wheezing following administration of FluMist. FluMist has not been studied in persons with severe asthma or active wheezing.

5.3 Guillain-Barré Syndrome

If Guillain-Barré syndrome (GBS) has occurred within 6 weeks of any prior influenza vaccination, the decision to give FluMist should be based on careful consideration of the potential benefits and potential risks.

The 1976 swine influenza vaccine (inactivated) was associated with an elevated risk of GBS. Evidence for causal relation of GBS with other influenza vaccines is inconclusive; if an excess risk exists, based on data for inactivated influenza vaccines, it is probably slightly more than 1 additional case per 1 million persons vaccinated1.

5.4 Altered Immunocompetence

The effectiveness of FluMist has not been studied in immunocompromised persons. Data on safety and shedding of vaccine virus after administration of FluMist in immunocompromised persons are limited to 173 persons with HIV infection and 10 mild to moderately immunocompromised children and adolescents with cancer [see Clinical Pharmacology (12.2)].

5.5 Medical Conditions Predisposing to Influenza Complications

The safety of FluMist in individuals with underlying medical conditions that may predispose them to complications following wild-type influenza infection has not been established.

5.6 Management of Acute Allergic Reactions

When administered by a healthcare provider in a healthcare setting, appropriate medical treatment must be immediately available to manage potential anaphylactic reactions following administration of FluMist [see Error! Hyperlink reference not valid.].

When FluMist is self-administered or administered by a caregiver, immediate medical attention should be sought if the vaccine recipient experiences symptoms of an allergic reaction following administration of FluMist.

5.7 Limitations of Vaccine Effectiveness

FluMist may not protect all individuals receiving the vaccine.

6 ADVERSE REACTIONS

The most common solicited adverse reactions (≥10% in vaccine recipients and at least 5% greater than in placebo recipients) reported after FluMist were runny nose or nasal congestion (ages 2 years through 49 years), fever over 100°F (children ages 2 years through 6 years), and sore throat (adults ages 18 years through 49 years).

6.1 Clinical Trials Experience

Because clinical trials are conducted under widely varying conditions, adverse reaction rates observed in the clinical trials of a vaccine cannot be directly compared to rates in the clinical trials of another vaccine and may not reflect the rates observed in practice.

A total of 9537 children and adolescents 1 through 17 years of age and 3041 adults 18 through 64 years of age received FluMist in randomized, placebo-controlled Studies D153-P501, AV006, D153-P526, AV019, and AV009 [3 used Allantoic Fluid containing Sucrose-Phosphate-Glutamate (AF-SPG) placebo, and 2 used saline placebo] described below. In addition, 4179 children 6 through 59 months of age received FluMist in Study MI-CP111, a randomized, active-controlled trial. Among pediatric FluMist recipients 6 months through 17 years of age, 50% were female; in the study of adults, 55% were female. In MI-CP111, AV006, D153-P526, AV019, and AV009, subjects were White (71%), Hispanic (11%), Asian (7%), Black (6%), and Other (5%), while in D153-P501, 99% of subjects were Asian.

FluMist in Children and Adolescents

The safety of FluMist was evaluated in an AF-SPG placebo-controlled Study (AV019) conducted in a Health Maintenance Organization (HMO) in children 1 through 17 years of age (FluMist = 6473, placebo = 3216). An increase in asthma events, captured by review of diagnostic codes, was observed in children younger than 5 years of age who received FluMist compared to those who received placebo (Relative Risk 3.53, 90% CI: 1.1, 15.7).

In Study MI-CP111, children 6 through 59 months of age were randomized to receive FluMist or inactivated Influenza Virus Vaccine manufactured by Sanofi Pasteur Inc. Wheezing requiring bronchodilator therapy or accompanied by respiratory distress or hypoxia was prospectively monitored from randomization through 42 days post last vaccination. Hospitalization due to all causes was prospectively monitored from randomization through 180 days post last vaccination. Increases in wheezing and hospitalization (for any cause) were observed in children 6 months through 23 months of age who received FluMist compared to those who received inactivated Influenza Virus Vaccine, as shown in Table 1.

Table 1: Percentages of Children with Hospitalizations and Wheezing from Study MI-CP111 [NCT00128167; see www.clinicaltrials.gov.]
Adverse Reaction | Age Group | FluMist (n/N) | Active Control [Inactivated Influenza Virus Vaccine manufactured by Sanofi Pasteur Inc., administered intramuscularly.] (n/N)
Hospitalizations [Hospitalization due to any cause from randomization through 180 days post last vaccination.] | 6-23 months | 4.2% (84/1992) | 3.2% (63/1975)
Hospitalizations [Hospitalization due to any cause from randomization through 180 days post last vaccination.] | 24-59 months | 2.1% (46/2187) | 2.5% (56/2198)
Wheezing [Wheezing requiring bronchodilator therapy or accompanied by respiratory distress or hypoxia evaluated from randomization through 42 days post last vaccination.] | 6-23 months | 5.9% (117/1992) | 3.8% (75/1975)
Wheezing [Wheezing requiring bronchodilator therapy or accompanied by respiratory distress or hypoxia evaluated from randomization through 42 days post last vaccination.] | 24-59 months | 2.1% (47/2187) | 2.5% (56/2198)

Most hospitalizations observed were due to gastrointestinal and respiratory tract infections and occurred more than 6 weeks post vaccination. In post-hoc analysis, rates of hospitalization in children 6 through 11 months of age were 6.1% (42/684) in FluMist recipients and 2.6% (18/683) in inactivated Influenza Virus Vaccine recipients.

Table 2 shows pooled solicited adverse reactions occurring in at least 1% of FluMist recipients and at a higher rate (≥1% rate difference after rounding) compared to placebo post Dose 1 for Studies D153-P501 and AV006, and solicited adverse reactions post Dose 1 for Study MI-CP111. Solicited adverse reactions were those about which parents/guardians were specifically queried after receipt of FluMist, placebo, or control vaccine. In these studies, solicited reactions were documented for 10 days post vaccination. Solicited reactions following the second dose of FluMist were similar to those following the first dose and were generally observed at a lower frequency.

Table 2: Summary of Solicited Adverse Reactions Observed Within 10 Days after Dose 1 for FluMist and Either Placebo or Active Control Recipients in Children 2 through 6 Years of Age
 | Studies D153-P501 [NCT00192244; see www.clinicaltrials.gov.] & AV006 |  | Study MI-CP111 [NCT00128167; see www.clinicaltrials.gov.]
 | FluMist | Placebo [Study D153-P501 used saline placebo; Study AV006 used AF-SPG placebo.] | FluMist | Active Control [Inactivated Influenza Virus Vaccine manufactured by Sanofi Pasteur Inc., administered intramuscularly.]
 | N = 876-1759 [Number of evaluable subjects (those who returned diary cards) for each reaction. Range reflects differences in data collection between the 2 pooled studies.] | N = 424-1034 | N = 2170 | N = 2165
Event | % | % | % | %
Runny Nose/ Nasal Congestion | 58 | 50 | 51 | 42
Decreased Appetite | 21 | 17 | 13 | 12
Irritability | 21 | 19 | 12 | 11
Decreased Activity (Lethargy) | 14 | 11 | 7 | 6
Sore Throat | 11 | 9 | 5 | 6
Headache | 9 | 7 | 3 | 3
Muscle Aches | 6 | 3 | 2 | 2
Chills | 4 | 3 | 2 | 2
Fever
> 100°F Oral > 100 - ≤ 101°F Oral > 101 - ≤ 102°F Oral | 16 9 4 | 11 6 3 | 13 6 4 | 11 4 3

In clinical studies D153-P501 and AV006, unsolicited adverse reactions in children occurring in at least 1% of FluMist recipients and at a higher rate (≥1% rate difference after rounding) compared to placebo were abdominal pain (2% FluMist vs. 0% placebo) and otitis media (3% FluMist vs. 1% placebo). An additional adverse reaction identified in the active-controlled trial MI-CP111 occurring in at least 1% of FluMist recipients and at a higher rate (≥1% rate difference after rounding) compared to active control was sneezing (2% FluMist vs.1% active control).

In a separate saline placebo-controlled trial (D153-P526) in a subset of older children and adolescents 9 through 17 years of age who received one dose of FluMist, the solicited adverse reactions as well as unsolicited adverse reactions reported were generally consistent with observations from the trials in Table 2. Abdominal pain was reported in 12% of FluMist recipients compared to 4% of placebo recipients and decreased activity was reported in 6% of FluMist recipients compared to 0% of placebo recipients.

In Study AV018, in which FluMist was concomitantly administered with Measles, Mumps, and Rubella Virus Vaccine Live (MMR, manufactured by Merck & Co., Inc.) and Varicella Virus Vaccine Live (manufactured by Merck & Co., Inc.) to children 12 through 15 months of age, adverse reactions were similar to those seen in other clinical trials of FluMist.

FluMist in Adults

In adults 18 through 49 years of age in Study AV009, solicited adverse reactions occurring in at least 1% of FluMist recipients and at a higher rate (≥1% rate difference after rounding) compared to AF-SPG placebo include runny nose (44% FluMist vs. 27% placebo), headache (40% FluMist vs. 38% placebo), sore throat (28% FluMist vs. 17% placebo), tiredness/weakness (26% FluMist vs. 22% placebo), muscle aches (17% FluMist vs. 15% placebo), cough (14% FluMist vs. 11% placebo), and chills (9% FluMist vs. 6% placebo).

In Study AV009, unsolicited adverse reactions occurring in at least 1% of FluMist recipients and at a higher rate (≥1% rate difference after rounding) compared to placebo were nasal congestion (9% FluMist vs. 2% placebo) and sinusitis (4% FluMist vs. 2% placebo).

6.2 Postmarketing Experience

The following events have been spontaneously reported during post approval use of FluMist or FluMist Quadrivalent. Data for FluMist Quadrivalent are relevant to FluMist because both vaccines are manufactured using the same process and have overlapping compositions. Because these events are reported voluntarily from a population of uncertain size, it is not always possible to reliably estimate their frequency or establish a causal relationship to vaccine exposure.

Cardiac disorders: Pericarditis

Congenital, familial, and genetic disorders: Exacerbation of symptoms of mitochondrial encephalomyopathy (Leigh syndrome)

Gastrointestinal disorders: Nausea, vomiting, diarrhea

Immune system disorders: Hypersensitivity reactions (including anaphylactic reaction, facial edema, and urticaria)

Nervous system disorders: Guillain-Barré syndrome, Bell’s Palsy, meningitis, eosinophilic meningitis, vaccine-associated encephalitis, syncope

Respiratory, thoracic, and mediastinal disorders: Epistaxis

Skin and subcutaneous tissue disorders: Rash

7 DRUG INTERACTIONS

7.1 Aspirin Therapy

Do not administer FluMist to children and adolescents through 17 years of age who are receiving aspirin therapy or aspirin-containing therapy because of the association of Reye’s syndrome with aspirin and wild-type influenza [see Contraindications (4.2)]. Avoid aspirin-containing therapy in these age groups during the first 4 weeks after vaccination with FluMist unless clearly needed.

7.2 Antiviral Agents Against Influenza A and/or B

Antiviral drugs that are active against influenza A and/or B viruses may reduce the effectiveness of FluMist if administered within 48 hours before, or within 2 weeks after vaccination. The concurrent use of FluMist with antiviral agents that are active against influenza A and/or B viruses has not been evaluated. If antiviral agents and FluMist are administered concomitantly, revaccination should be considered when appropriate.

8 USE IN SPECIFIC POPULATIONS

8.1 Pregnancy

Risk Summary

FluMist is not absorbed systemically following intranasal administration and maternal use is not expected to result in fetal exposure to the drug.

8.2 Lactation

Risk Summary

FluMist is not absorbed systemically by the mother following intranasal administration and breastfeeding is not expected to result in exposure of the child to FluMist.

8.4 Pediatric Use

FluMist is not approved for use in children younger than 24 months of age because use of FluMist in children 6 through 23 months has been associated with increased risks of hospitalization and wheezing in clinical trials [see Warnings and Precautions (5.1) and Adverse Reactions (6.1)].

The effectiveness of FluMist in children 6 years through 17 years of age is supported by demonstration of efficacy in younger children 6 through 71 months of age and effectiveness in adults 18 through 49 years of age [see Clinical Studies (14)].

8.5 Geriatric Use

FluMist is not approved for use in persons 65 years of age and older because in a clinical study (AV009), effectiveness of FluMist to prevent febrile illness was not demonstrated in adults 50 through 64 years of age [see Clinical Studies (14.2)]. In this study, solicited events among individuals 50 through 64 years of age were similar in type and frequency to those reported in younger adults. In a clinical study of FluMist in persons 65 years of age and older, subjects with underlying high-risk medical conditions (N = 200) were studied for safety. Compared to controls, FluMist recipients had a higher rate of sore throat.

11 DESCRIPTION

FluMist (Influenza Vaccine Live, Intranasal) is a nasal spray. FluMist contains three vaccine virus strains: an A/H1N1 strain, an A/H3N2 strain and a B strain from the B/Victoria lineage.

The influenza virus strains in FluMist are (a) cold-adapted (ca) (i.e., they replicate efficiently at 25°C, a temperature that is restrictive for replication of many wild-type influenza viruses); (b) temperature-sensitive (ts) (i.e., they are restricted in replication at 37°C (Type B strain) or 39°C (Type A strains), temperatures at which many wild-type influenza viruses grow efficiently); and (c) attenuated (att) (i.e., they do not produce classic influenza-like illness in the ferret model of human influenza infection).

No evidence of reversion has been observed in the recovered vaccine strains that have been tested (135 of possible 250 recovered isolates) using FluMist [see Clinical Pharmacology (12.2)]. For each of the three reassortant strains in FluMist, the six internal gene segments responsible for ca, ts, and att phenotypes are derived from a master donor virus (MDV), and the two segments that encode the two surface glycoproteins, hemagglutinin (HA) and neuraminidase (NA), are derived from the corresponding antigenically relevant wild-type influenza viruses. Thus, the three viruses contained in FluMist maintain the replication characteristics and phenotypic properties of the MDV and express the HA and NA of wild-type viruses. For the Type A MDV, at least five genetic loci in three different internal gene segments contribute to the ts and att phenotypes. For the Type B MDV, at least three genetic loci in two different internal gene segments contribute to both the ts and att properties; five genetic loci in three gene segments control the ca property.

Each of the reassortant strains in FluMist express the HA and NA of wild- type viruses that are related to strains expected to circulate during the 2025-2026 influenza season. The viruses (A/H1N1, A/H3N2 and the B strain) have been recommended by the United States Public Health Service (USPHS) for inclusion in the annual trivalent influenza vaccine formulation.

Specific pathogen-free (SPF) eggs are inoculated with each of the reassortant strains and incubated to allow vaccine virus replication. The allantoic fluid of these eggs is harvested, pooled, and then clarified by filtration. The virus is concentrated by ultracentrifugation and diluted with stabilizing buffer to obtain the final sucrose and potassium phosphate concentrations. The viral harvests are then sterile filtered to produce the monovalent bulks. Each lot is tested for ca, ts, and att phenotypes and is also tested extensively by in vitro and in vivo methods to detect adventitious agents. Monovalent bulks from the three strains are subsequently blended and diluted as required to attain the desired potency with stabilizing buffers to produce the trivalent bulk vaccine. The bulk vaccine is then filled directly into individual sprayers for nasal administration.

Each pre-filled refrigerated FluMist sprayer contains a single 0.2 mL dose. Each 0.2 mL dose contains 10^6.5-7.5 FFU (fluorescent focus units) of live attenuated influenza virus reassortants of each of the three strains: A/Norway/31694/2022 (H1N1) (an A/Victoria/4897/2022 (H1N1)pdm09 - like virus), A/Perth/722/2024 (H3N2) (an A/Croatia/10136RV/2023 (H3N2) - like virus), and B/Austria/1359417/2021 (B/Victoria lineage) (a B/Austria/1359417/2021 (B/Victoria lineage) - like virus). Each 0.2 mL dose also contains 0.188 mg/dose monosodium glutamate, 2.00 mg/dose hydrolyzed porcine gelatin, 2.42 mg/dose arginine, 13.68 mg/dose sucrose, 2.26 mg/dose dibasic potassium phosphate, and 0.96 mg/dose monobasic potassium phosphate. Each dose contains residual amounts of ovalbumin (<0.024 mcg/dose), and may also contain residual amounts of gentamicin sulfate (<0.015 mcg/mL), and ethylenediaminetetraacetic acid (EDTA) (< 2.3 mcg/dose). FluMist contains no preservatives.

The tip attached to the sprayer is equipped with a nozzle that produces a fine mist that is primarily deposited in the nose and nasopharynx. FluMist is a colorless to pale yellow suspension and is clear to slightly cloudy.

12 CLINICAL PHARMACOLOGY

12.1 Mechanism of Action

Immune mechanisms conferring protection against influenza following receipt of FluMist vaccine are not fully understood; serum antibodies, mucosal antibodies, and influenza-specific T cells may play a role.

FluMist contains live attenuated influenza viruses that must infect and replicate in cells lining the nasopharynx of the recipient to induce immunity. Vaccine viruses capable of infection and replication can be cultured from nasal secretions obtained from vaccine recipients (shedding) [see Clinical Pharmacology (12.2)].

12.2 Pharmacodynamics

Shedding Studies

Shedding of vaccine viruses within 28 days of vaccination with FluMist was evaluated in (1) multi-center Study MI‑CP129 which enrolled healthy individuals 6 through 59 months of age (N = 200); and (2) multi-center Study FM026 which enrolled healthy individuals 5 through 49 years of age (N = 344). In each study, nasal secretions were obtained daily for the first 7 days and every other day through either Day 25 and on Day 28 or through Day 28. In Study MI‑CP129, individuals with a positive shedding sample at Day 25 or Day 28 were to have additional shedding samples collected every 7 days until culture negative on 2 consecutive samples. Results of these studies are presented in Table 3.

Table 3: Characterization of Shedding with FluMist in Specified Age Groups by Frequency, Amount, and Duration (Study MI-CP129 [NCT00344305; see www.clinicaltrials.gov.] and Study FM026 [NCT00192140; see www.clinicaltrials.gov.])
Age | Number of Subjects | % Shedding [Proportion of subjects with detectable virus at any time point during the 28 days.] | Peak Titer (TCID50/mL) [Peak titer at any time point during the 28 days among samples positive for a single vaccine virus.] | % Shedding After Day 11 | Day of Last Positive Culture
6-23 months [FluMist is not approved for use in children younger than 24 months of age [see Adverse Reactions (6.1)].] 24-59 months 5-8 years 9-17 years 18-49 years | 99 100 102 126 115 | 89 69 50 29 20 | < 5 log10 < 5 log10 < 5 log10 < 4 log10 < 3 log10 | 7.0 1.0 2.9 1.6 0.9 | Day 23 [A single subject who shed previously on Days 1-3; TCID50/mL was less than 1.5 log10 on Day 23.] Day 25 [A single subject who did not shed previously; TCID50/mL was less than 1.5 log10.] Day 23 [A single subject who did not shed previously; TCID50/mL was less than 1.0 log10.] Day 28 Day 17

The highest proportion of subjects in each group shed one or more vaccine strains on Days 2-3 post vaccination. After Day 11 among individuals 2 through 49 years of age (n = 443), virus titers did not exceed 1.5 log10 TCID50/mL.

Studies in Immunocompromised Individuals

Safety and shedding of vaccine virus following FluMist administration were evaluated in 28 HIV‑infected adults [median CD4 cell count of 541 cells/mm^3] and 27 HIV-negative adults 18 through 58 years of age. No serious adverse events were reported during the one-month follow-up period. Vaccine strain (type B) virus was detected in 1 of 28 HIV-infected subjects on Day 5 only, and in none of the HIV-negative FluMist recipients.

Safety and shedding of vaccine virus following FluMist administration were also evaluated in children in a randomized (1:1), cross-over, double-blind, AF-SPG placebo-controlled trial in 24 HIV-infected children [median CD4 cell count of 1013 cells/mm^3] and 25 HIV-negative children 1 through 7 years of age, and in a randomized (1:1), open-label, inactivated influenza vaccine-controlled trial in 243 HIV-infected children and adolescents 5 through 17 years of age receiving stable anti-retroviral therapy. Frequency and duration of vaccine virus shedding in HIV-infected individuals were comparable to that seen in healthy individuals. No adverse effects on HIV viral load or CD4 counts were identified following FluMist administration. In the 5 through 17 year old age group, one inactivated influenza vaccine recipient and one FluMist recipient experienced pneumonia within 28 days of vaccination (days 17 and 13, respectively). The effectiveness of FluMist in preventing influenza illness in HIV-infected individuals has not been evaluated.

Twenty mild to moderately immunocompromised children and adolescents 5 through 17 years of age (receiving chemotherapy and/or radiation therapy or who had received chemotherapy in the 12 weeks prior to enrollment) were randomized 1:1 to receive FluMist or AF-SPG placebo. Frequency and duration of vaccine virus shedding in these immunocompromised children and adolescents were comparable to that seen in healthy children and adolescents. The effectiveness of FluMist in preventing influenza illness in immunocompromised individuals has not been evaluated.

Transmission Study

A prospective, randomized, double-blind, placebo-controlled trial was performed in a daycare setting in children younger than 3 years of age to assess the transmission of vaccine viruses from a vaccinated individual to a non-vaccinated individual. A total of 197 children 8 through 36 months of age were randomized to receive one dose of FluMist (N = 98) or AF-SPG placebo (N = 99). Virus shedding was evaluated for 21 days by culture of nasal swab specimens. Wild-type A (A/H3N2) influenza virus was documented to have circulated in the community and in the study population during the trial, whereas Type A (A/H1N1) and Type B strains did not.

At least one vaccine strain was isolated from 80% of FluMist recipients; strains were recovered from 1-21 days post vaccination (mean duration of 7.6 days ± 3.4 days). The ca and ts phenotypes were preserved in 135 tested of 250 strains isolated at the local laboratory. Ten influenza isolates (9 influenza A, 1 influenza B) were cultured from a total of seven placebo subjects. One placebo subject had mild symptomatic Type B virus infection confirmed as a transmitted vaccine virus by a FluMist recipient in the same playgroup. This Type B isolate retained the ca, ts, and att phenotypes of the vaccine strain and had the same genetic sequence when compared to a Type B virus cultured from a vaccine recipient within the same playgroup. Four of the influenza Type A isolates were confirmed as wild-type A/Panama (H3N2). The remaining isolates could not be further characterized.

Assuming a single transmission event (isolation of the Type B vaccine strain), the probability of a young child acquiring vaccine virus following close contact with a single FluMist vaccinee in this daycare setting was 0.58% (95% CI: 0, 1.7) based on the Reed-Frost model. With documented transmission of one Type B in one placebo subject and possible transmission of Type A viruses in four placebo subjects, the probability of acquiring a transmitted vaccine virus was estimated to be 2.4% (95% CI: 0.13, 4.6) using the Reed-Frost model.

13 NONCLINICAL TOXICOLOGY

13.1 Carcinogenesis, Mutagenesis, Impairment of Fertility

FluMist has not been evaluated for its carcinogenic or mutagenic potential.

14 CLINICAL STUDIES

14.1 Efficacy Studies of FluMist in Children

A multi-national, randomized, double-blind, active-controlled trial (MI-CP111) was performed to assess the efficacy of FluMist compared to an intramuscularly administered, inactivated Influenza Virus Vaccine manufactured by Sanofi Pasteur Inc. (active control) in children 6 months to less than 5 years of age during the 2004-2005 influenza season. A total number of 3916 children without severe asthma, without use of bronchodilator or steroids, and without wheezing within the prior 6 weeks were randomized to FluMist and 3936 were randomized to active control. Children who previously received any influenza vaccine received a single dose of study vaccine, while those who never previously received an influenza vaccination (or had an unknown history of influenza vaccination) received two doses. Participants were then followed through the influenza season to identify illness caused by influenza virus. As the primary endpoint, culture-confirmed modified CDC-ILI (CDC-defined influenza-like illness) was defined as a positive culture for a wild-type influenza virus associated within ±7 days of modified CDC-ILI. Modified CDC-ILI was defined as fever (temperature ≥100°F oral or equivalent) with cough, sore throat, or runny nose/nasal congestion on the same or consecutive days.

In the primary efficacy analysis, FluMist demonstrated a 44.5% (95% CI: 22.4, 60.6) reduction in influenza rate compared to active control as measured by culture-confirmed modified CDC-ILI caused by wild-type strains antigenically similar to those contained in the vaccine. See Table 4 for a description of the results by strain and antigenic similarity.

Table 4: Comparative Efficacy Against Culture-Confirmed Modified CDC-ILI [Modified CDC-ILI was defined as fever (temperature ≥ 100°F oral or equivalent) plus cough, sore throat, or runny nose/nasal congestion on the same or consecutive days.] Caused by Wild-Type Strains (Study MI-CP111) [In children 6 months through 5 years of age.] [NCT00128167; see www.clinicaltrials.gov.]
 | FluMist |  |  | Active Control [Inactivated Influenza Virus Vaccine manufactured by Sanofi Pasteur Inc., administered intramuscularly.] |  |  | % Reduction in Rate for FluMist [Reduction in rate was adjusted for country, age, prior influenza vaccination status, and wheezing history status.] | 95% CI
 | N | # of Cases | Rate (cases/N) | N | # of Cases | Rate (cases/N) | % Reduction in Rate for FluMist [Reduction in rate was adjusted for country, age, prior influenza vaccination status, and wheezing history status.] | 95% CI
Matched Strains
All strains | 3916 | 53 | 1.4% | 3936 | 93 | 2.4% | 44.5% | 22.4, 60.6
A/H1N1 | 3916 | 3 | 0.1% | 3936 | 27 | 0.7% | 89.2% | 67.7, 97.4
A/H3N2 | 3916 | 0 | 0.0% | 3936 | 0 | 0.0% | -- | --
B | 3916 | 50 | 1.3% | 3936 | 67 | 1.7% | 27.3% | -4.8, 49.9
Mismatched Strains
All strains | 3916 | 102 | 2.6% | 3936 | 245 | 6.2% | 58.2% | 47.4, 67.0
A/H1N1 | 3916 | 0 | 0.0% | 3936 | 0 | 0.0% | -- | --
A/H3N2 | 3916 | 37 | 0.9% | 3936 | 178 | 4.5% | 79.2% | 70.6, 85.7
B | 3916 | 66 | 1.7% | 3936 | 71 | 1.8% | 6.3% | -31.6, 33.3
Regardless of Match
All strains | 3916 | 153 | 3.9% | 3936 | 338 | 8.6% | 54.9% | 45.4, 62.9
A/H1N1 | 3916 | 3 | 0.1% | 3936 | 27 | 0.7% | 89.2% | 67.7, 97.4
A/H3N2 | 3916 | 37 | 0.9% | 3936 | 178 | 4.5% | 79.2% | 70.6, 85.7
B | 3916 | 115 | 2.9% | 3936 | 136 | 3.5% | 16.1% | -7.7, 34.7
ATP Population.

A randomized, double-blind, saline placebo-controlled trial (D153-P501) was performed to evaluate the efficacy of FluMist in children 12 through 35 months of age without high-risk medical conditions against culture-confirmed influenza illness. This study was performed in Asia over two successive seasons (2000-2001 and 2001-2002). The primary endpoint of the trial was the prevention of culture-confirmed influenza illness due to antigenically matched wild-type influenza. Respiratory illness that prompted an influenza culture was defined as at least one of the following: fever (≥100.4°F rectal or ≥99.5°F axillary), wheezing, shortness of breath, pulmonary congestion, pneumonia, or otitis media; or two of the following: runny nose/nasal congestion, sore throat, cough, muscle aches, chills, headache, irritability, decreased activity, or vomiting. A total of 3174 children were randomized 3:2 (vaccine:placebo) to receive 2 doses of study vaccine or placebo at least 28 days apart in Year 1. See Table 5 for a description of the results.

During the second year of Study D153-P501, for children who received two doses in Year 1 and one dose in Year 2, FluMist demonstrated 84.3% (95% CI: 70.1, 92.4) efficacy against culture-confirmed influenza illness due to antigenically matched wild-type influenza.

Study AV006 was a second multi-center, randomized, double-blind, AF-SPG placebo-controlled trial performed in U.S. children without high-risk medical conditions to evaluate the efficacy of FluMist against culture-confirmed influenza over two successive seasons (1996-1997 and 1997-1998). The primary endpoint of the trial was the prevention of culture-confirmed influenza illness due to antigenically matched wild-type influenza in children who received two doses of vaccine in the first year and a single revaccination dose in the second year. Respiratory illness that prompted an influenza culture was defined as at least one of the following: fever (≥101°F rectal or oral; or ≥100.4°F axillary), wheezing, shortness of breath, pulmonary congestion, pneumonia, or otitis media; or two of the following: runny nose/nasal congestion, sore throat, cough, muscle aches, chills, headache, irritability, decreased activity, or vomiting. During the first year of the study, 1602 children 15 through 71 months of age were randomized 2:1 (vaccine:placebo). See Table 5 for a description of the results.

Table 5: Efficacy [D153-P501 and AV006 data are for subjects who received two doses of study vaccine.] of FluMist vs. Placebo Against Culture-Confirmed Influenza Illness Due to Antigenically Matched Wild-Type Strains (Studies D153-P501 [In children 12 through 35 months of age.] & AV006 [In children 15 through 71 months of age.] , Year 1)
 | D153-P501 [NCT00192244; see www.clinicaltrials.gov.] |  |  | AV006 [NCT00192179; see www.clinicaltrials.gov.]
 | FluMist n [Number and percent of subjects in per-protocol efficacy analysis population with culture-confirmed influenza illness.] (%) | Placebo n (%) | % Efficacy (95% CI) | FluMist n (%) | Placebo n (%) | % Efficacy (95% CI)
 | N [Number of subjects in per-protocol efficacy analysis population of each treatment group of each study for the “any strain” analysis.] = 1653 | N = 1111 |  | N = 849 | N = 410
Any strain | 56 (3.4%) | 139 (12.5%) | 72.9% [For D153-P501, influenza circulated through 12 months following vaccination.] (62.8, 80.5) | 10 (1%) | 73 (18%) | 93.4% (87.5, 96.5)
A/H1N1 | 23 (1.4%) | 81 (7.3%) | 80.9% (69.4, 88.5) [Estimate includes A/H1N1 and A/H1N2 strains. Both were considered antigenically similar to the vaccine.] | 0 | 0 | --
A/H3N2 | 4 (0.2%) | 27 (2.4%) | 90.0% (71.4, 97.5) | 4 (0.5%) | 48 (12%) | 96.0% (89.4, 98.5)
B | 29 (1.8%) | 35 (3.2%) | 44.3% (6.2, 67.2) | 6 (0.7%) | 31 (7%) | 90.5% (78.0, 95.9)

During the second year of Study AV006, children remained in the same treatment group as in Year 1 and received a single dose of FluMist or placebo. During the second year, the primary circulating strain was the A/Sydney/05/97 H3N2 strain, which was antigenically dissimilar from the H3N2 strain represented in the vaccine, A/Wuhan/359/95; FluMist demonstrated 87.0% (95% CI: 77.0, 92.6) efficacy against culture-confirmed influenza illness.

14.2 Effectiveness Study of FluMist in Adults

AV009 was a U.S. multi-center, randomized, double-blind, AF-SPG placebo-controlled trial to evaluate effectiveness of FluMist in adults 18 through 64 years of age without high-risk medical conditions over the 1997-1998 influenza season. Participants were randomized 2:1 (vaccine:placebo). Cultures for influenza virus were not obtained from subjects in the trial, thus efficacy against culture-confirmed influenza was not assessed. The A/Wuhan/359/95 (H3N2) strain, which was contained in FluMist, was antigenically distinct from the predominant circulating strain of influenza virus during the trial period, A/Sydney/05/97 (H3N2). Type A/Wuhan (H3N2) and Type B strains also circulated in the U.S. during the study period. The primary endpoint of the trial was the reduction in the proportion of participants with one or more episodes of any febrile illness, and prospective secondary endpoints were severe febrile illness and febrile upper respiratory illness. Effectiveness for any of the three endpoints was not demonstrated in a subgroup of adults 50 through 64 years of age. Primary and secondary effectiveness endpoints from the age group 18 through 49 years are presented in Table 6. Effectiveness was not demonstrated for the primary endpoint in adults 18 through 49 years of age.

Table 6: Effectiveness of FluMist to Prevent Febrile Illness in Adults 18 through 49 Years of Age During the 7-Week Site-Specific Outbreak Period (Study AV009)
Endpoint | FluMist N = 2411 [Number of evaluable subjects (92.7% and 93.0% of FluMist and placebo recipients, respectively).] n (%) | Placebo N = 1226 n (%) | Percent Reduction | (95% CI)
Participants with one or more events of: [The predominantly circulating virus during the trial period was A/Sydney/05/97 (H3N2), an antigenic variant not included in the vaccine.] Primary Endpoint: Any febrile illness Secondary Endpoints: Severe febrile illness Febrile upper respiratory illness | 331 (13.73) 250 (10.37) 213 (8.83) | 189 (15.42) 158 (12.89) 142 (11.58) | 10.9 19.5 23.7 | (-5.1, 24.4) (3.0, 33.2) (6.7, 37.5)

Effectiveness was shown in a post-hoc analysis using an endpoint of CDC-ILI in the age group 18 through 49 years of age.

14.3 Concomitantly Administered Live Virus Vaccines

In Study AV018, concomitant administration of FluMist, MMR (manufactured by Merck & Co., Inc.) and Varicella Virus Vaccine Live (manufactured by Merck & Co., Inc.) was studied in 1245 subjects 12 through 15 months of age. Subjects were randomized in a 1:1:1 ratio to MMR, Varicella vaccine and AF-SPG placebo (group 1); MMR, Varicella vaccine and FluMist (group 2); or FluMist alone (group 3). Immune responses to MMR and Varicella vaccines were evaluated 6 weeks post-vaccination while the immune responses to FluMist were evaluated 4 weeks after the second dose. No evidence of interference with immune response to measles, mumps, rubella, varicella and FluMist vaccines was observed.

15 REFERENCES

1. Lasky T, Terracciano GJ, Magder L, et al. The Guillain-Barré syndrome and the 1992 – 1993 and 1993 – 1994 influenza vaccines. N Engl J Med 1998;339(25):1797-802.

16 HOW SUPPLIED/STORAGE AND HANDLING

16.1 How Supplied

FluMist is supplied in a single-dose (0.2 mL) intranasal sprayer. The single-use intranasal sprayer is not made with natural rubber latex.

Single intranasal sprayer: NDC 66019-112-00

Carton containing 1 intranasal sprayer: NDC 66019-112-51

Carton containing 10 intranasal sprayers: NDC 66019-112-10

16.2 Storage and Handling

FLUMIST SHOULD BE STORED IN A REFRIGERATOR BETWEEN 2-8°C (35-46°F) UPON RECEIPT. THE PRODUCT MUST NOT BE USED AFTER THE EXPIRATION DATE ON THE SPRAYER LABEL.

DO NOT FREEZE.

Keep FluMist sprayer in outer carton in order to protect from light.

A single temperature excursion up to 25°C (77°F) for 12 hours has been shown to have no adverse impact on the vaccine. After a temperature excursion, the vaccine should be returned immediately to the recommended storage condition (2°C – 8°C [35 – 46°F]) and used as soon as feasible. Subsequent excursions are not permitted.

In a healthcare setting, when FluMist has been administered or has expired, the sprayer should be disposed of according to the standard procedures for medical waste (e.g., sharps container or biohazard container). Instruct vaccine recipients or caregivers who administer FluMist to follow the directions provided in the “Instructions for Use” for disposal of FluMist.

17 PATIENT COUNSELING INFORMATION

When FluMist is self-administered or administered by a caregiver, instruct the vaccine recipient or caregiver to read the “Instructions for Use.” Individuals 2 through 17 years of age should not self‑administer FluMist.

Advise the vaccine recipient or caregiver to read the FDA-approved patient labeling (Information for Patients and Their Caregivers).

Provide the Vaccine Information Statements (VIS) which are required by the National Childhood Vaccine Injury Act of 1986 to be given with each immunization.

Dosing in Children 2 through 8 years of age

Inform the caregiver of the need for two doses at least 1 month apart in children 2 through 8 years of age, depending on vaccination history.

Asthma and Recurrent Wheezing

Ask if the vaccine recipient has asthma. For children younger than 5 years of age, also ask if the vaccine recipient has recurrent wheezing since this may be an asthma equivalent in this age group. Inform the vaccine recipient or caregiver that there may be an increased risk of wheezing associated with FluMist in persons younger than 5 years of age with recurrent wheezing and persons of any age with asthma [see Warnings and Precautions (5.2)].

Vaccination with a Live Virus Vaccine

Inform the vaccine recipient or caregiver that FluMist is an attenuated live virus vaccine and has the potential for transmission to immunocompromised household contacts.

Acute Allergic Reactions

Instruct the vaccine recipient or caregiver to seek immediate medical attention if the vaccine recipient experiences any symptoms of an acute allergic reaction [see Warnings and Precautions (5.6)].

Adverse Event Reporting

Instruct the vaccine recipient or caregiver to report adverse reactions to their healthcare provider.

FluMist® is a registered trademark of MedImmune, LLC.

Manufactured by:

MedImmune, LLC

Gaithersburg, MD 20878

1-877-633-4411

U.S. Government License No. 1799

Issue Date: August 2025

Patient Package Insert

Information for Patients and Their Caregivers

FluMist® (FLEW-mĭst)

(Influenza Vaccine Live, Intranasal)

Please read this Patient Information carefully before getting FluMist.

This is a summary of information about FluMist. It does not take the place of talking with your healthcare provider about influenza vaccination. If you have questions or would like more information, please talk with your healthcare provider.

What is FluMist?

FluMist is a vaccine that is sprayed into the nose to help protect against influenza. It can be used in children, adolescents, and adults ages 2 through 49 years. FluMist may not prevent influenza in everyone who gets vaccinated.

Who should not get FluMist?

You should not get FluMist if you:

- have a severe allergy to eggs or to any inactive ingredient in the vaccine (see “What are the ingredients in FluMist?”)
- have ever had a severe allergic reaction to influenza vaccinations.
- are 2 through 17 years of age and take aspirin or medicines containing aspirin. Children or adolescents should not be given aspirin for 4 weeks after getting FluMist unless your healthcare provider tells you otherwise.

Please talk to your healthcare provider if you are not sure if the items listed above apply to you or your child.

Children under 2 years of age have an increased risk of wheezing (difficulty with breathing) after getting FluMist.

Before getting FluMist, tell your healthcare provider about all your medical conditions, including if you:

- are currently wheezing
- have a history of wheezing and are under 5 years of age
- have asthma
- have had Guillain-Barré syndrome
- have a weakened immune system or live with someone who has a severely weakened immune system
- have problems with your heart, kidneys, or lungs
- have diabetes
- are pregnant or nursing
- are taking antiviral drugs for the treatment of influenza

If you or your child cannot get FluMist, you may still be able to get an influenza vaccine. Talk to your healthcare provider about this.

How is FluMist given?

- FluMist is a liquid that is sprayed into the nose.
- You can breathe normally while getting FluMist. There is no need to inhale or sniff it.
- People 9 years of age and older need one dose of FluMist each year.
- Children 2 through 8 years of age may need 2 doses of FluMist, depending on their history of previous influenza vaccination. Your healthcare provider will decide if your child needs a second dose.

If you are giving FluMist to yourself or someone else, read the “Instructions for Use” that comes with FluMist. Individuals 2 through 17 years of age should not give themselves FluMist.

What are the possible side effects of FluMist?

There is a very small chance that FluMist could cause a severe allergic reaction. A severe allergic reaction would usually occur within a few minutes to one hour after getting a dose. Seek medical attention right away if you experience:

- hives (itchy, raised bumps on the skin)
- severe flushing of the skin
- throat tightness
- trouble swallowing or speaking
- trouble breathing or wheezing

- swelling of the face, lips, eyes, tongue, or throat
- chest discomfort or tightness
- dizziness or fainting
- severe stomach cramps or pain, vomiting or diarrhea

The most common side effects are:

- runny or stuffy nose
- sore throat

- fever over 100°F

Other possible side effects include:

- decreased appetite
- irritability
- tiredness
- cough

- headache
- muscle ache
- chills

These are not all the possible side effects of FluMist. For more information, talk to your healthcare provider.

Call your healthcare provider for medical advice about side effects. You may report side effects to VAERS at 1-800-822-7967 or http://vaers.hhs.gov.

What are the ingredients in FluMist?

Active Ingredient: FluMist contains 3 influenza virus strains that are weakened (A(H1N1), A(H3N2), and B Victoria lineage).

Inactive Ingredients: FluMist also contains monosodium glutamate, gelatin, arginine, sucrose, dibasic potassium phosphate, monobasic potassium phosphate, and gentamicin.

FluMist does not contain preservatives.

How is FluMist stored?

If you are giving FluMist to yourself or someone else, read the storage information in the “Instructions for Use” that comes with FluMist.

Keep FluMist out of the reach of children.

If you would like more information about FluMist, talk to your healthcare provider or visit www.FluMist.com or call 1-877-633-4411.

FluMist® is a registered trademark of MedImmune, LLC.

Other brands listed are registered trademarks of their respective owners and are not trademarks of MedImmune, LLC.

Manufactured by:

MedImmune, LLC

Gaithersburg, MD 20878

Issue date: August 2025

RAL-FLUV16

This Patient Information has been approved by the U.S. Food and Drug Administration.

Issued: August 2025

INSTRUCTIONS FOR USE

FluMist® (FLEW-mĭst)

(Influenza Vaccine Live, Intranasal)

Nasal Spray

This Instructions for Use contains information on how to use FluMist. Even if you have previously used FluMist, there may be new information. This information does not take the place of talking to a healthcare provider about whether to use FluMist.

If you or your caregiver have any questions, talk to a healthcare provider or call MedImmune information center 1-877-633-4411.

Unfold to view full Instructions for Use

Each FluMist Nasal Sprayer Contains 1 Dose (2 Sprays)

1 Dose = 2 Sprays

1 spray for each nostril.

IMPORTANT:

DO NOT remove the dose divider clip

until Spray 2 (Step 9).

Important Information You Need to Know Before Using FluMist

- A caregiver should administer FluMist to individuals 2 through 17 years of age.
- DO NOT use FluMist if:
  ‒ It has been frozen.
  ‒ It has been dropped and/or damaged.
  ‒ The carton has been opened, damaged, or appears tampered with.
  ‒ The expiration date (EXP) has passed.

If any of the above happens, follow Step 13 and contact MedImmune or your healthcare provider.

- DO NOT use FluMist in the eyes, mouth, or on your skin.
- DO NOT share FluMist with anyone or reuse the sprayer.
- DO NOT inject FluMist.

Contact MedImmune or your healthcare provider if you have any questions.

Storing FluMist

- Keep FluMist and all medicines out of reach of children.
- Store FluMist in a refrigerator between 35°F to 46°F (2°C to 8°C) in its carton to protect from light until you are ready to use it.
- FluMist may be kept at room temperature between 68°F to 77°F (20°C to 25°C) in its carton for a maximum of 12 hours.
- DO NOT freeze FluMist.
- DO NOT expose FluMist to temperatures greater than 77°F (25°C).

Preparing to Use FluMist

Remove the FluMist carton from the refrigerator and place on a clean flat surface.

- Use FluMist within 12 hours of removing from the refrigerator.

Check the carton.

- DO NOT use FluMist if the expiration (EXP) date has passed.
- DO NOT use if the carton has been opened, damaged, or appears tampered with.

Open the carton and remove the FluMist sprayer by holding onto the sprayer body.

- DO NOT hold the sprayer by any other parts.

Check the FluMist sprayer.

- DO NOT use FluMist if the expiration (EXP) date on the label has passed or if the sprayer appears damaged.

Check the liquid in the sprayer.

- The liquid should be colorless to pale yellow and clear to slightly cloudy.
- DO NOT use if the liquid appears discolored.
- DO NOT attempt to remove bubbles from the sprayer.

Spray 1

Hold on to the sprayer body and pull off the gray cap.

- DO NOT remove the dose divider clip until Step 9.
- DO NOT push or pull the plunger.
- DO NOT prime or remove bubbles from the sprayer.
- DO NOT insert the sprayer into nostril before removing the cap.

Keeping head in upright position, place just the sprayer tip inside one nostril. The sprayer tip does not need to be inserted far into the nose.

- DO NOT insert the entire white tip inside the nostril.

Administer Spray 1 by pushing the plunger as quickly as possible until it stops at the dose divider clip.

- DO NOT remove sprayer until the plunger has stopped.
- DO NOT remove the dose divider clip until Step 9.
- Breathe normally. There is no need to inhale or sniff.
- It is normal if you feel a slight tickle or experience some dripping or sneezing.

Remove the sprayer from the first nostril.

- Wipe away any liquid that drips from the nose with a tissue.

IMPORTANT:

Continue to Spray 2 (Step 9) to remove the dose divider clip.

Spray 2

Holding onto the sprayer body, pinch and remove the dose divider clip from plunger.

- DO NOT push or pull the plunger.

Keeping head in upright position, place just the sprayer tip inside the other nostril. The sprayer tip does not need to be inserted far into the nose.

- DO NOT insert the entire white tip inside the nostril.

Administer Spray 2 by pushing the plunger as quickly as possible until it stops.

- DO NOT remove sprayer until the plunger has stopped.
- Breathe normally. There is no need to inhale or sniff.
- It is normal if you feel a slight tickle or experience some dripping or sneezing.

Remove the sprayer from the second nostril.

- Wipe away any liquid that drips from the nose with a tissue.

Dispose of used sprayer through return shipment program.

Follow the return shipment program steps outlined in the separate directions that were provided with your FluMist dose.

- FluMist contains a single dose and cannot be reused.
- DO NOT dispose of your used sprayer in your household trash.

If you or your caregiver have any questions, talk to your healthcare provider or call 1-877-633-4411.

Manufactured by: MedImmune, LLC, Gaithersburg, MD 20878

U.S. Government License No. 1799

This Instructions for Use has been approved by the U.S. Food and Drug Administration.

Approved: September 2024

PACKAGE/LABEL PRINCIPAL DISPLAY PANEL

2025-2026 FORMULA

Influenza Vaccine Live, Intranasal

FluMist®

STORE REFRIGERATED

at 2º-8ºC (35º-46ºF)

RX only

For 2-49 years of age

PROTECT FROM LIGHT

FOR INTRANASAL USE

Contents: 10 pre-filled sprayers

One 0.2 mL dose each

(0.1 mL per nostril)

Manufactured by MedImmune, LLC.

One MedImmune Way

Gaithersburg, MD 20878 USA

U.S. Govt. License No. 1799

Product of the United Kingdom

MedImmune

Package/Label Display Panel

2025-2026 FORMULA

Influenza Vaccine Live, Intranasal

FluMist®

FOR INTRANASAL USE

1 nasal sprayer containing 1 dose.

1 dose is 2 sprays (1 spray for each nostril).

STORE FluMist sprayer refrigerated

at 35ºF to 46ºF (2ºC to 8ºC) in

original carton to protect from light.

Do not freeze. Do not expose

to temperatures greater than 77ºF (25ºC).

Keep out of reach of children.

Manufactured by MedImmune, LLC.

One MedImmune Way

Gaithersburg, MD 20878 USA

U.S. Govt. License No. 1799

Product of the United Kingdom

MedImmune